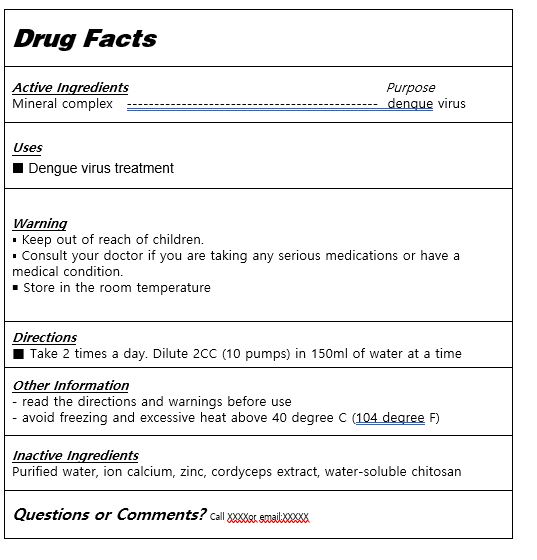 DRUG LABEL: Dengue Kill
NDC: 81016-0007 | Form: LIQUID
Manufacturer: AML Bio Co., Ltd.
Category: otc | Type: HUMAN OTC DRUG LABEL
Date: 20240123

ACTIVE INGREDIENTS: ATORVASTATIN CALCIUM ANHYDROUS 3 g/100 mL
INACTIVE INGREDIENTS: WATER

Drug Facts

ACTIVE INGREDIENT

mineral complex

PURPOSE

dengue virus

KEEP OUT OF REACH OF THE CHILDREN

INDICATIONS AND USAGE

Take 2 times a day. Dilute 2CC (10 pumps) in 150ml of water at a time

▪ Keep out of reach of children.

▪ Consult your doctor if you are taking any serious medications or have a medical condition.

￭ Store in the room temperature

DOSAGE AND ADMINISTRATION

for oral use only

INACTIVE INGREDIENT

Purified water, ion calcium, zinc, cordyceps extract, water-soluble chitosan